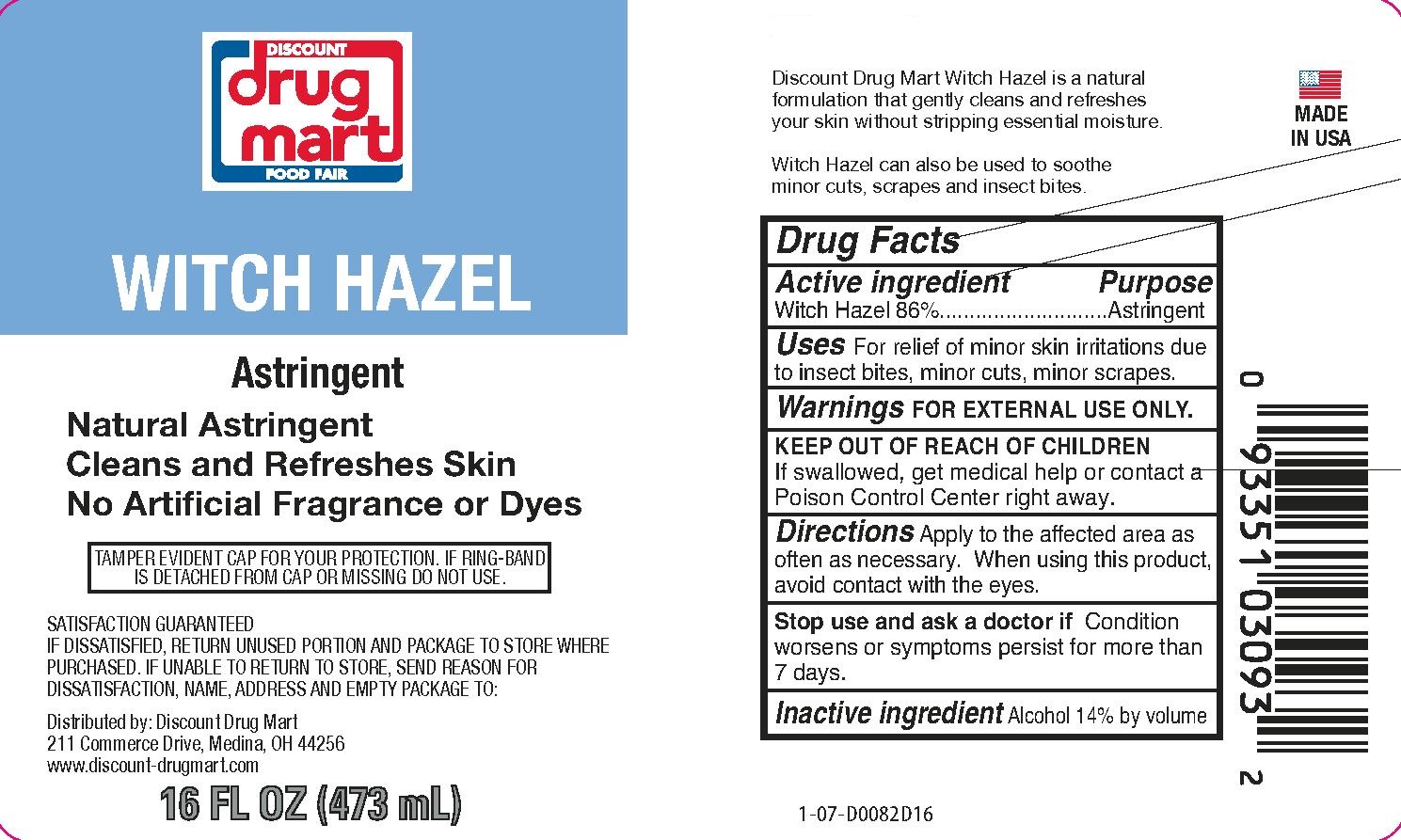 DRUG LABEL: Witch Hazel
NDC: 53943-555 | Form: LIQUID
Manufacturer: Discount Drug Mart
Category: otc | Type: HUMAN OTC DRUG LABEL
Date: 20241114

ACTIVE INGREDIENTS: WITCH HAZEL 86 mg/100 mL
INACTIVE INGREDIENTS: ALCOHOL

Witch Hazel

Active Ingredient

Witch Hazel 86%

Purpose

Astringent

Uses: Relieves minor skin irritation due to:

- insect bites
- minor cuts
- minor scrapes

Warnings

For external use only

When using this product

- Avoid contact with eyes. If contact occurs, rinse thoroughly with water.

Stop use and ask a doctor if

- Condition worsens or symptoms persist for more than 7 days.

Keep out of reach of children.

- If swallowed, get medical help or contact a Poison Control Center right away.

Directions

- After cleansing apply generously to cotton ball and gently wipe skin.
- Apply as often as needed.

Inactive ingredients

Alcohol 14% by volume.

Principal Display Panel

Discount Drug Mart

Witch Hazel

ASTRINGENT

Natural Astringent

Cleans and Refreshes Skin

No Artificial Fragrance or Dyes

TAMPER EVIDENT CAP FOR YOUR PROTECTION.

IF RING-BAND IS DETATCHED FROM CAP OR MISSING, DO NOT USE.

SATISFACTION GUARANTEED

IF DISSATISFIED, RETURN UNUSED PORTION AND PACKAGE TO STORE WHERE PURCHASED.

IF UNABLE TO RETURN TO STORE, SEND REASON FOR DISSATISFACTION,

NAME, ADDRESS AND EMPTY PACKAGE TO:

Distributed by: Discount Drug Mart

211 Commerce Drive, Medina, OH 44256

www.discount-drugmart.com

16 FL OZ (473 mL)